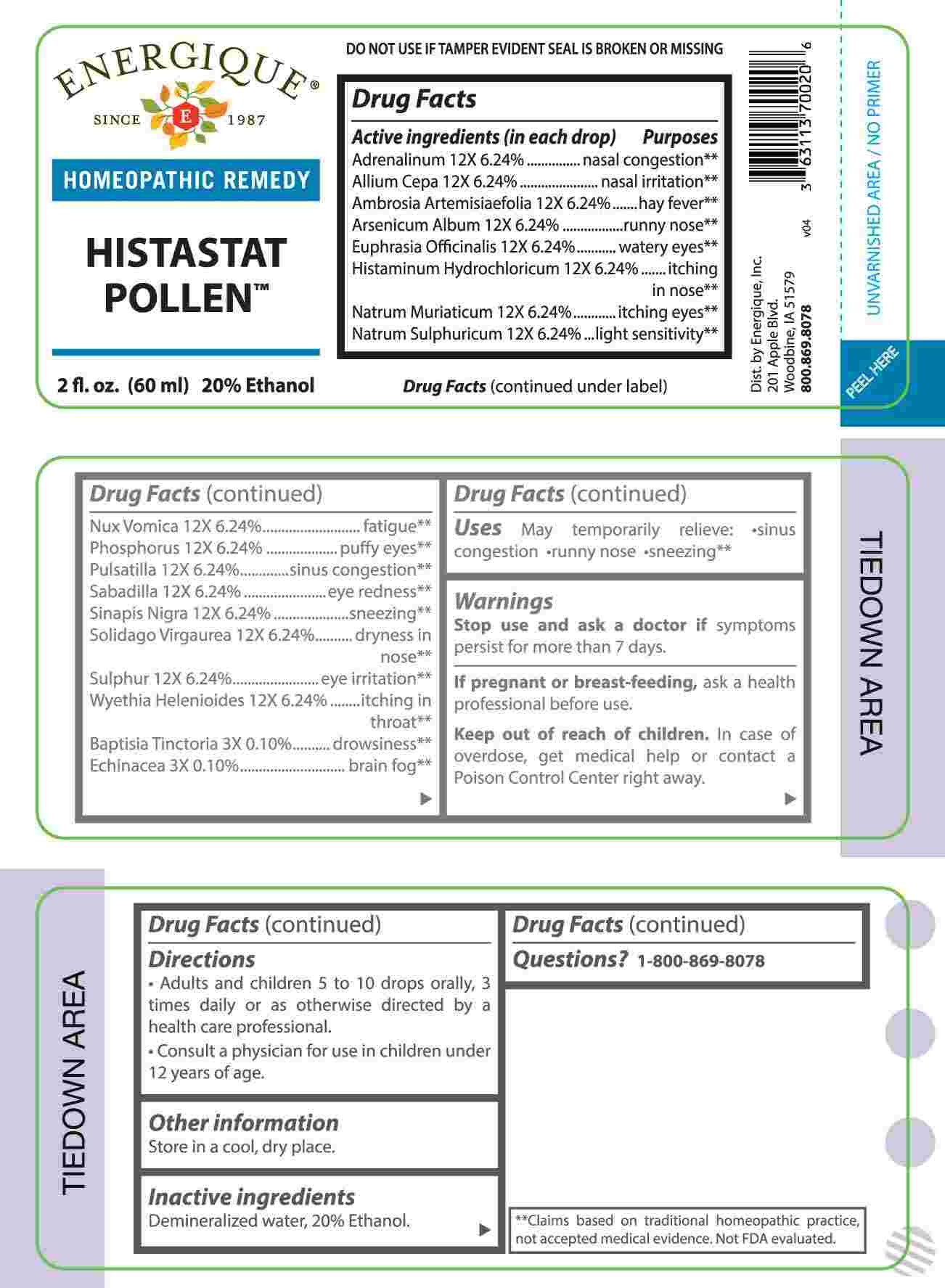 DRUG LABEL: Histastat Pollen
NDC: 44911-0730 | Form: LIQUID
Manufacturer: Energique, Inc.
Category: homeopathic | Type: HUMAN OTC DRUG LABEL
Date: 20250127

ACTIVE INGREDIENTS: BAPTISIA TINCTORIA ROOT 3 [hp_X]/1 mL; ECHINACEA ANGUSTIFOLIA WHOLE 3 [hp_X]/1 mL; EPINEPHRINE 12 Ci/1 mL; ONION 12 [hp_X]/1 mL; AMBROSIA ARTEMISIIFOLIA WHOLE 12 [hp_X]/1 mL; ARSENIC TRIOXIDE 12 [hp_X]/1 mL; EUPHRASIA STRICTA 12 [hp_X]/1 mL; HISTAMINE DIHYDROCHLORIDE 12 [hp_X]/1 mL; SODIUM CHLORIDE 12 [hp_X]/1 mL; SODIUM SULFATE 12 [hp_X]/1 mL; STRYCHNOS NUX-VOMICA SEED 12 [hp_X]/1 mL; PHOSPHORUS 12 [hp_X]/1 mL; PULSATILLA PRATENSIS WHOLE 12 [hp_X]/1 mL; SCHOENOCAULON OFFICINALE SEED 12 [hp_X]/1 mL; BLACK MUSTARD SEED 12 [hp_X]/1 mL; SOLIDAGO VIRGAUREA FLOWERING TOP 12 [hp_X]/1 mL; SULFUR 12 [hp_X]/1 mL; WYETHIA HELENIOIDES ROOT 12 [hp_X]/1 mL
INACTIVE INGREDIENTS: WATER; ALCOHOL

DRUG FACTS:

ACTIVE INGREDIENTS:

(in each drop): Adrenalinum 12X 6.24%, Allium Cepa 12X 6.24%, Ambrosia Artemisiaefolia 12X 6.24%, Arsenicum Album 12X 6.24%, Euphrasia Officinalis 12X 6.24%, Histaminum Hydrochloricum 12X 6.24%, Natrum Muriaticum 12X 6.24%, Natrum Sulphuricum 12X 6.24%, Vox Vomica 12X 6.24%, Phosphorus 12X 6.24%, Pulsatilla 12X 6.24%, Sabadilla 12X 6.24%, Sinapis Nigra 12X 6.24%, Solidago Virgaurea 12X 6.24%, Sulphur 12X 6.24%, Wyethia Helenioides 12X 6.24%, Baptisia Tinctoria 3X 0.10%, Echinacea 3X 0.10%.

PURPOSE:

Adrenalinum – nasal congestion,** Allium Cepa – nasal irritation,** Ambrosia Artemisiaefolia – hay fever,** Arsenicum Album – runny nose,** Euphrasia Officinalis – watery eyes,** Histaminum Hydrochloricum – itching in nose,** Natrum Muriaticum – itching eyes,** Natrum Sulphuricum – light sensitivity,** Vox Vomica - fatigue,** Phosphorus – puffy eyes,** Pulsatilla – sinus congestion,** Sabadilla – eye redness,** Sinapis Nigra - sneezing,** Solidago Virgaurea – dryness in nose,** Sulphur – eye irritation,** Wyethia Helenioides – itching in throat,** Baptisia Tinctoria - drowsiness,** Echinacea – brain fog**

**Claims based on traditional homeopathic practice, not accepted medical evidence. Not FDA evaluated.

USES:

May temporarily relieve:

•sinus congestion •runny nose •sneezing**

**Claims based on traditional homeopathic practice, not accepted medical evidence. Not FDA evaluated.

WARNINGS:

Stop use and ask a doctor if symptoms persist for more than 7 days.

If pregnant or breast-feeding, ask a health professional before use.

Keep out of reach of children. In case of overdose, get medical help or contact a Poison Control Center right away.

DO NOT USE IF TAMPER EVIDENT SEAL IS BROKEN OR MISSING

Store in a cool, dry place.

KEEP OUT OF REACH OF CHILDREN:

In case of overdose, get medical help or contact a Poison Control Center right away.

DIRECTIONS:

• Adults and children 5 to 10 drops orally, 3 times daily or as otherwise directed by a health care professional.

Consult a physician for use in children under 12 years of age.

INACTIVE INGREDIENTS:

Demineralized water, 20% Ethanol.

QUESTIONS:

Dist. by Energique, Inc.

201 Apple Blvd.

Woodbine, IA 51579

800-869-8078

PACKAGE LABEL DISPLAY:

ENERGIQUE

SINCE 1987

HOMEOPATHIC REMEDY

HISTASTAT POLLEN

2 fl. oz. (60 ml)